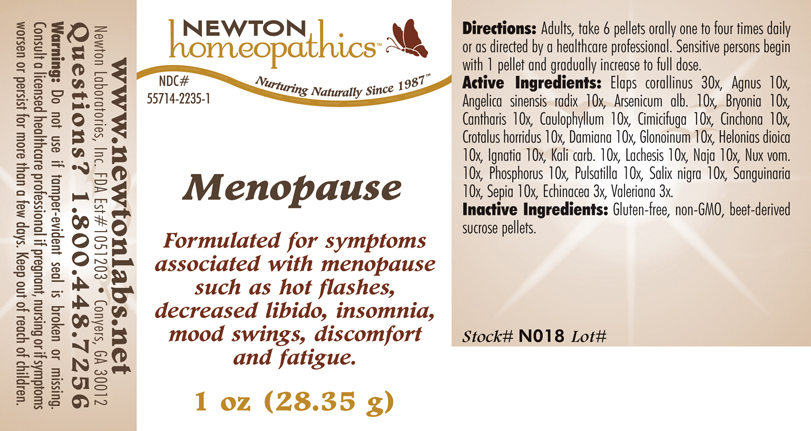 DRUG LABEL: Menopause 
NDC: 55714-2235 | Form: PELLET
Manufacturer: Newton Laboratories, Inc.
Category: homeopathic | Type: HUMAN OTC DRUG LABEL
Date: 20110301

ACTIVE INGREDIENTS: Micrurus Corallinus Venom 30 [hp_X]/1 g; Chaste Tree 10 [hp_X]/1 g; Angelica Sinensis Root 10 [hp_X]/1 g; Arsenic Trioxide 10 [hp_X]/1 g; Bryonia Alba Root 10 [hp_X]/1 g; Lytta Vesicatoria 10 [hp_X]/1 g; Caulophyllum Thalictroides Root 10 [hp_X]/1 g; Black Cohosh 10 [hp_X]/1 g; Cinchona Officinalis Bark 10 [hp_X]/1 g; Crotalus Horridus Horridus Venom 10 [hp_X]/1 g; Turnera Diffusa Leafy Twig 10 [hp_X]/1 g; Nitroglycerin 10 [hp_X]/1 g; Chamaelirium Luteum Root 10 [hp_X]/1 g; Strychnos Ignatii Seed 10 [hp_X]/1 g; Potassium Carbonate 10 [hp_X]/1 g; Lachesis Muta Venom 10 [hp_X]/1 g; Naja Naja Venom 10 [hp_X]/1 g; Strychnos Nux-vomica Seed 10 [hp_X]/1 g; Phosphorus 10 [hp_X]/1 g; Pulsatilla Vulgaris 10 [hp_X]/1 g; Salix Nigra Bark 10 [hp_X]/1 g; Sanguinaria Canadensis Root 10 [hp_X]/1 g; Sepia Officinalis Juice 10 [hp_X]/1 g; Echinacea, Unspecified 3 [hp_X]/1 g; Valerian 3 [hp_X]/1 g
INACTIVE INGREDIENTS: Sucrose

Menopause

INDICATIONS & USAGE SECTION

Menopause Formulated for symptoms associated with menopause such as hot flashes, decreased libido, insomnia, mood swings, discomfort and fatigue.

DOSAGE & ADMINISTRATION SECTION

Directions: Adults, take 6 pellets orally one to four times daily or as directed by a healthcare professional. Sensitive persons begin with 1 pellet and gradually increase to full dose.

OTC - ACTIVE INGREDIENT SECTION

Elaps corallinus 30x, Agnus 10x, Angelica sinensis radix 10x, Arsenicum alb. 10x, Bryonia 10x, Cantharis 10x, Caulophyllum 10x, Cimicifuga 10x, Cinchona 10x, Crotalus horridus 10x, Damiana 10x, Glonoinum 10x, Helonias dioica 10x, Ignatia 10x, Kali carb. 10x, Lachesis 10x, Naja 10x, Nux vom.10x, Phosphorus 10x, Pulsatilla 10x, Salix nigra 10x, Sanguinaria 10x, Sepia 10x, Echinacea 3x, Valeriana 3x.

OTC - PURPOSE SECTION

Formulated for symptoms associated with menopause such as hot flashes, decreased libido, insomnia, mood swings, discomfort and fatigue.

INACTIVE INGREDIENT SECTION

Inactive Ingredients: Gluten-free, non-GMO, beet-derived sucrose pellets.

QUESTIONS SECTION

www.newtonlabs.net Newton Laboratories, Inc. FDA Est # 1051203 - Conyers, GA 30012
Questions? 1.800.448.7256

WARNINGS SECTION

Warning: Do not use if tamper - evident seal is broken or missing. Consult a licensed healthcare professional if pregnant, nursing or if symptoms worsen or persist for more than a few days. Keep out of reach of children.

OTC - PREGNANCY OR BREAST FEEDING SECTION

Consult a licensed healthcare professional if pregnant, nursing or if symptoms worsen or persist for more than a few days.

OTC - KEEP OUT OF REACH OF CHILDREN SECTION

Keep out of reach of children